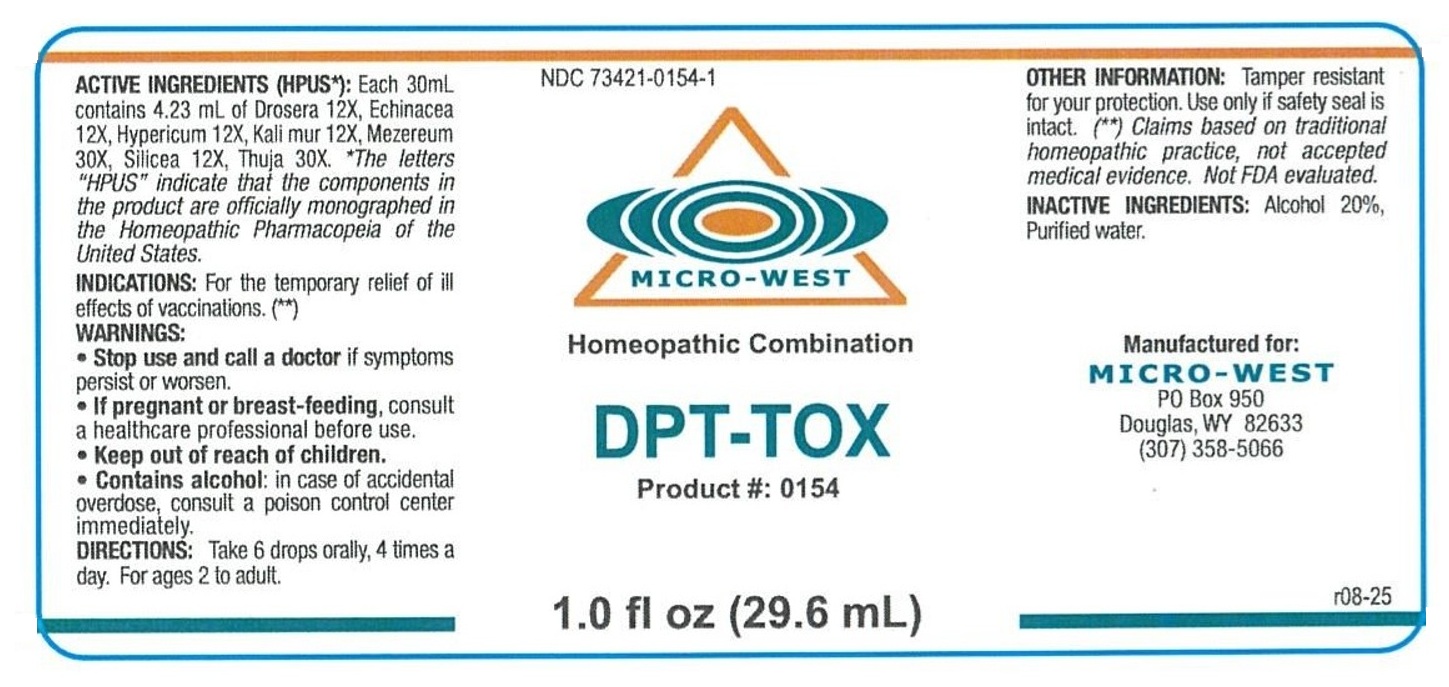 DRUG LABEL: DPT-TOX
NDC: 73421-0154 | Form: SOLUTION/ DROPS
Manufacturer: Nutrition Center Inc dba Nutri-West dba Micro-West
Category: homeopathic | Type: HUMAN OTC DRUG LABEL
Date: 20260204

ACTIVE INGREDIENTS: DROSERA ROTUNDIFOLIA WHOLE 12 [hp_X]/30 mL; ECHINACEA, UNSPECIFIED 12 [hp_X]/30 mL; ST. JOHN'S WORT 12 [hp_X]/30 mL; POTASSIUM CHLORIDE 12 [hp_X]/30 mL; DAPHNE MEZEREUM BARK 30 [hp_X]/30 mL; SILICON DIOXIDE 12 [hp_X]/30 mL; THUJA OCCIDENTALIS LEAFY TWIG 30 [hp_X]/30 mL
INACTIVE INGREDIENTS: ALCOHOL; WATER

DPT-TOX

ACTIVE INGREDIENTS (HPUS*):

Each 30mL contains 4.23 mL of Drosera 12X, Echinacea 12X, Hypericum 12X, Kali mur 12X, Mezereum 30X, Silicea 12X, Thuja 30X.

*The letters "HPUS" indicate that the components in the product are officially monographed in the Homeopathic Pharmacopeia of the United States.

(**) Claims based on traditional homeopathic practice, not accepted medical evidence. Not FDA evaluated.

PURPOSE:

For the temporary relief of ill effects of vaccinations. (**)

INDICATIONS:

For the temporary relief of ill effects of vaccinations. (**)

WARNINGS:

- Stop use and call a doctor if symptoms persist or worsen.
- If pregnant or breast-feeding, consult a healthcare professional before use.

- Keep out of reach of children.
- Contains alcohol: in case of accidental overdose, consult a poison control center immediately.

DIRECTIONS:

Take 6 drops orally, 4 times a day. For ages 2 to adult.

OTHER INFORMATION:

Tamper resistant for your protection. Use only if safety seal is intact.

INACTIVE INGREDIENTS:

Alcohol 20%, Purified water.

MICRO-WEST

Homeopathic Combination

Manufactured for:
MICRO-WEST
PO Box 950
Douglas, WY 82633
(307) 358-5066